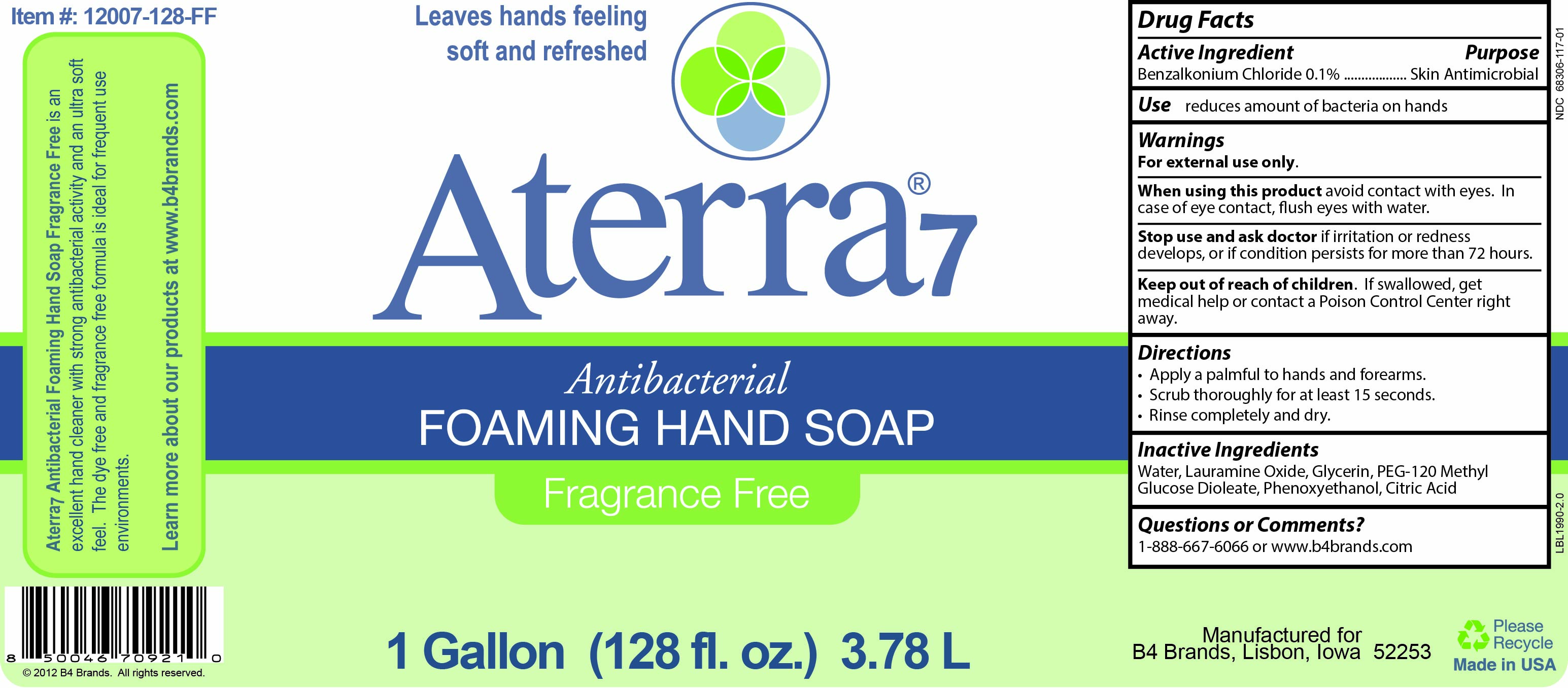 DRUG LABEL: Aterra7 Antibacterial Foaming Hand
NDC: 68306-117 | Form: SOLUTION
Manufacturer: B4 Ventures LLC
Category: otc | Type: HUMAN OTC DRUG LABEL
Date: 20250609

ACTIVE INGREDIENTS: BENZALKONIUM CHLORIDE 1 mg/1 mL
INACTIVE INGREDIENTS: LAURAMINE OXIDE; PEG-120 METHYL GLUCOSE DIOLEATE; WATER; GLYCERIN; CITRIC ACID MONOHYDRATE; PHENOXYETHANOL

Aterra7 Antibacterial Foaming Hand Soap

Active Ingredient

Benzalkonium Chloride 0.1%

Purpose

Skin Antimicrobial

Use

reduces amount of bacteria on hands

Warnings

For external use only.

When using this product avoid contact with eyes. In case of eye contact, flush eyes with water.

Stop use and ask doctor if irritation or redness develops, or if condition persists for more than 72 hours.

Keep out of reach of children. If swallowed, get medical help or contact a Poison Control Center right away.

Directions

- Apply a palmful to hands and forearms.
- Scrub thoroughly for at least 15 seconds.
- Rinse completely and dry.

Inactive Ingredients

Water, Lauramine Oxide, Glycerin, PEG-120 Methyl Glucose Dioleate, Phenoxyethanol, Citric Acid

Questions or Comments?

1-888-667-6066 or www.b4brands.com